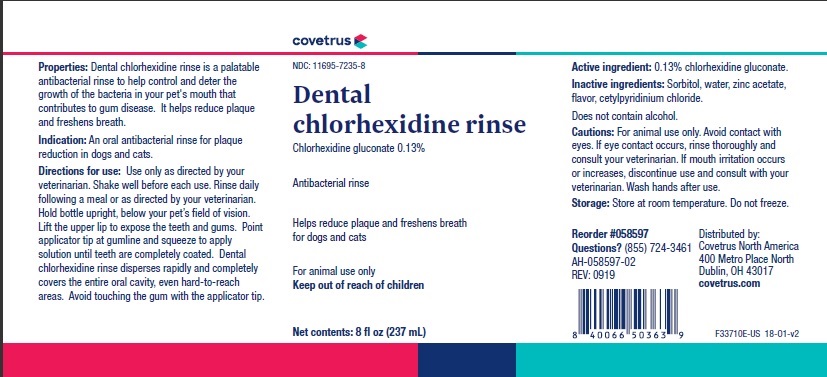 DRUG LABEL: Dental
NDC: 11695-7235 | Form: RINSE
Manufacturer: Butler Animal Health Supply, LLC dba Covetrus North America
Category: animal | Type: OTC ANIMAL DRUG LABEL
Date: 20191218

ACTIVE INGREDIENTS: CHLORHEXIDINE GLUCONATE 1.3 mg/1 mL
INACTIVE INGREDIENTS: SORBITOL; WATER; ZINC ACETATE; CETYLPYRIDINIUM CHLORIDE

DESCRIPTION

Dental chlorhexidine rinse

Active ingredient: 0.13% chlorhexidine gluconate.

Inactive ingredients: Sorbitol, water, zinc acetate, flavor, cetylpyridinium chloride.

Does not contain alcohol.

Properties: Dental chlorhexidine rinse is a palatable antibacterial rinse to help control and deter the growth of the bacteria in your pet's mouth that contributes to gum disease. It helps reduce plaque and freshens breath.

INDICATIONS AND USAGE

Indication: An oral antibacterial rinse for plaque reduction in dogs and cats.

Directions for use: Use only as directed by your veterinarian. Shake well before each use. Rinse daily following a meal or as directed by your veterinarian. Hold bottle upright, below your pet’s field of vision. Lift the upper lip to expose the teeth and gums. Point applicator tip at gumline and squeeze to apply solution until teeth are completely coated. Dental chlorhexidine rinse disperses rapidly and completely covers the entire oral cavity, even hard-to-reach areas. Avoid touching the gum with the applicator tip.

WARNINGS AND PRECAUTIONS

Cautions: For animal use only. Avoid contact with eyes. If eye contact occurs, rinse thoroughly and consult your veterinarian. If mouth irritation occurs or increases, discontinue use and consult with your veterinarian. Wash hands after use.

Storage: Store at room temperature. Do not freeze.

Questions? Questions? (855) 724-3461

Covetrus North America
400 Metro Place North
Dublin, OH 43017
covetrus.com

PRINCIPAL DISPLAY PANEL - 8 OUNCE (237 mL) Bottle

covetrus

NDC: 11695-7235-8

Dental

chlorhexidine rinse

Chlorhexidine Gluconate 0.13%

Antibacterial rinse

Helps reduce plaque and freshens breath

for dogs and cats

For animal use only

Keep out of reach of children

Net contents: 8 fl oz (237 mL)